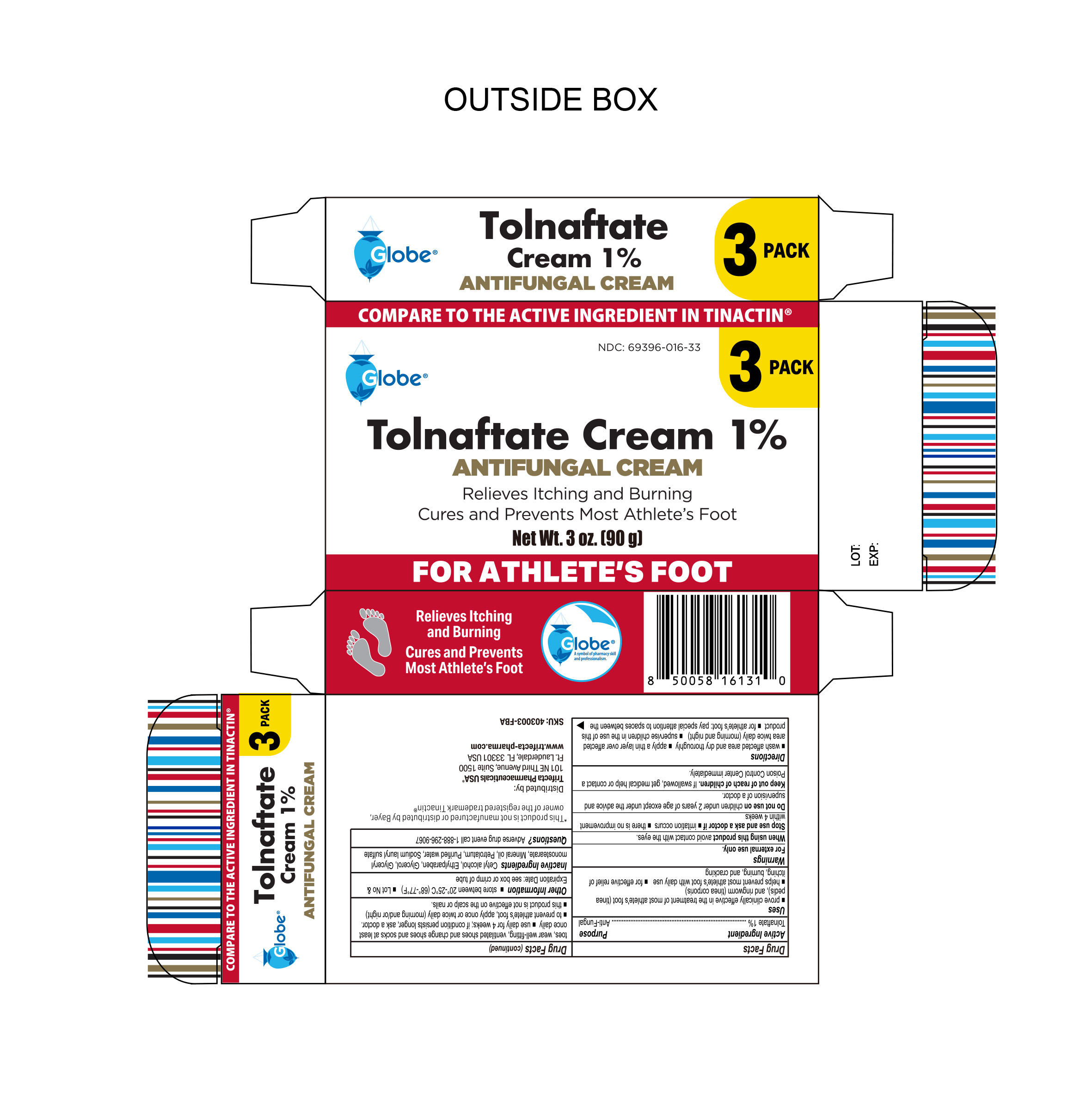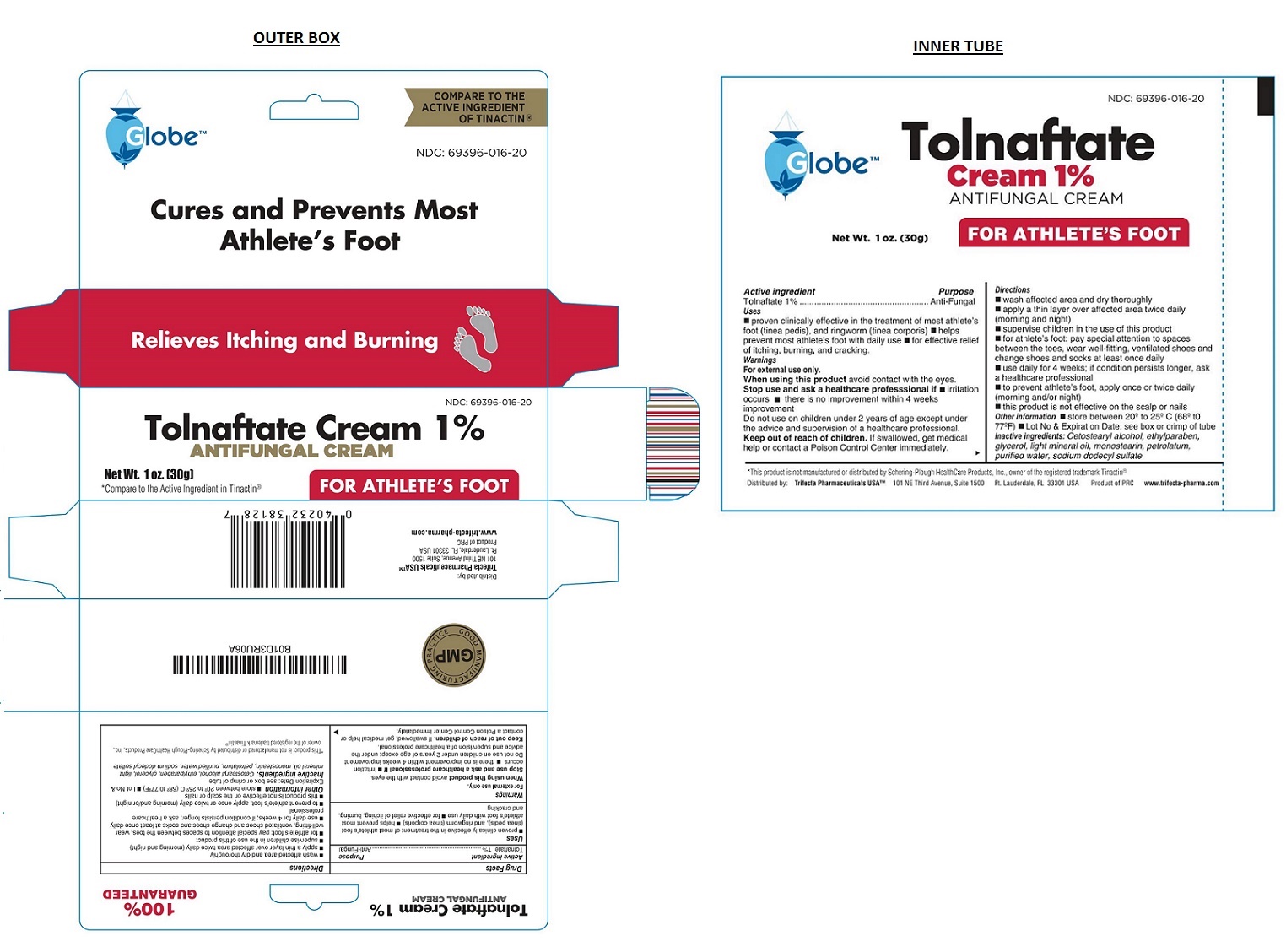 DRUG LABEL: Tolnaftate Cream 1% ANTIFUNGAL
NDC: 69396-016 | Form: CREAM
Manufacturer: Trifecta Pharmaceuticals Usa Llc
Category: otc | Type: HUMAN OTC DRUG LABEL
Date: 20250515

ACTIVE INGREDIENTS: TOLNAFTATE 1 g/100 g
INACTIVE INGREDIENTS: CETOSTEARYL ALCOHOL; ETHYLPARABEN; GLYCERIN; LIGHT MINERAL OIL; GLYCERYL MONOSTEARATE; PETROLATUM; WATER; SODIUM LAURYL SULFATE

Tolnaftate Cream 1% ANTIFUNGAL CREAM

Active ingredient

Tolnaftate 1%

Purpose

Anti-Fungal

Keep out of reach of children. If swallowed, get medical help or contact a Poison Control Center immediately.

Uses

● proven clinically effective in the treatment of most athlete's foot (tinea pedis), and ringworm (tinea corporis) ● helps prevent most athlete's foot with daily use ● for effective relief of itching, burning and cracking.

Warnings

For external use only.

When using this product avoid contact with the eyes.

Stop use and ask a healthcare professional if ● irritation occurs ● there is no improvement within 4 weeks improvement

Do not use on children under 2 years of age except under the advice and supervision of a healthcare professional.

Directions

● wash affected area and dry thoroughly

● apply a thin layer over affected area twice daily (morning and night)

● supervise children in the use of this product

● for athlete’s foot: pay special attention to spaces between the toes, wear well-fitting ventilated shoes and change shoes and socks at least once daily.

● use daily for 4 weeks; if conditions persists longer, ask a healthcare professional.

● to prevent athlete's foot, apply once or twice daily (morning and/or night)

● this product is not effective on the scalp or nails.

Inactive ingredients

Cetostearyl alcohol, ethylparaben, glycerol, light mineral oil, monostearin, petrolatum, purified water, sodium dodecyl sulfate

Other information

● store between 20° to 25°C (68° to 77°F) ● Lot No & Expiration Date: See box or crimp of tube.

100% GUARANTEED

Cures and Prevents Most Athlete's Foot

Distributed by:

Trifecta Pharmaceuticals USA™

101 NE Third Avenue, Suite 1500

Ft. Lauderdale, FL 33301 USA

Product of PRC

www.trifecta-pharma.com